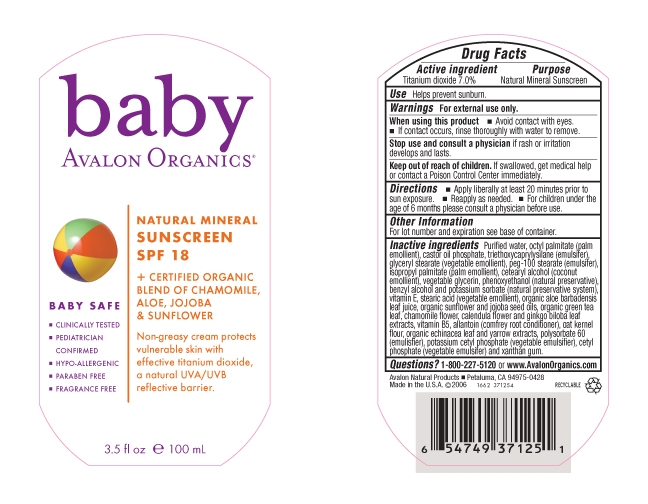 DRUG LABEL: AV3712501 Mineral Sunscreen SPF 18
NDC: 61995-1125 | Form: CREAM
Manufacturer: The Hain Celestial Group, Inc.
Category: prescription | Type: HUMAN PRESCRIPTION DRUG LABEL
Date: 20110323

ACTIVE INGREDIENTS: Titanium Dioxide 7.0 g/100 g

Drug Facts

ACTIVE INGREDIENT

Titanium Dioxide 7.0%

USAGE

- Helps prevent sunburn
- Apply liberally at least 20 minutes prior to sun exposure
- Reapply as needed
- For children under the age of 6 months please contact physician before use

WARNINGS and PRECAUTIONS

For external use only.

When using this product avoid contact with eyes. If contact occurs, rinse throughly with water to remove.

Stop use and consult a physician if rash or irritation develops and lasts.

Keep out of reach of children. If swallowed, get medical help or contact Poison Control Center immediately.

QUESTIONS?

1-800-227-5120 or www.AvalonOrganics.com